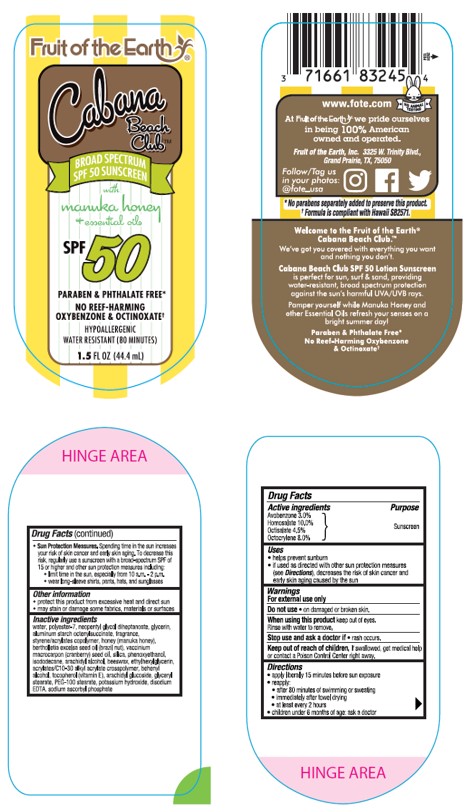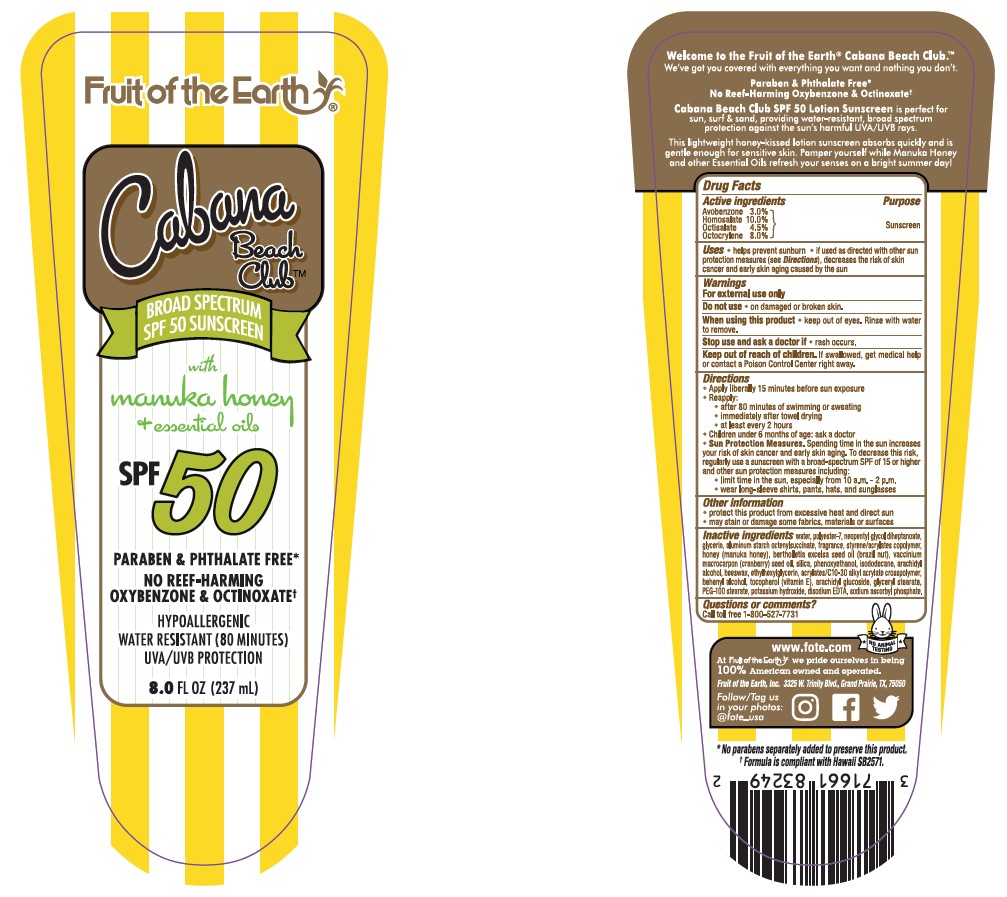 DRUG LABEL: Cabana Beach Club with Manuka Honey and Essential Oils SPF 50 Sunscreen
NDC: 62217-245 | Form: LOTION
Manufacturer: Fruit of the Earth, Inc.
Category: otc | Type: HUMAN OTC DRUG LABEL
Date: 20241018

ACTIVE INGREDIENTS: AVOBENZONE 30 mg/1 mL; HOMOSALATE 100 mg/1 mL; OCTISALATE 45 mg/1 mL; OCTOCRYLENE 80 mg/1 mL
INACTIVE INGREDIENTS: WATER; GLYCERIN; POLYESTER-7; NEOPENTYL GLYCOL DIHEPTANOATE; ALUMINUM STARCH OCTENYLSUCCINATE; SILICON DIOXIDE; PHENOXYETHANOL; ISODODECANE; ARACHIDYL ALCOHOL; ETHYLHEXYLGLYCERIN; CARBOMER COPOLYMER TYPE A; DOCOSANOL; .ALPHA.-TOCOPHEROL, DL-; WHITE WAX; ARACHIDYL GLUCOSIDE; POTASSIUM HYDROXIDE; GLYCERYL 1-STEARATE; PEG-100 STEARATE; EDETATE DISODIUM; SODIUM ASCORBYL PHOSPHATE; BUTYL METHACRYLATE/METHYL METHACRYLATE/METHACRYLIC ACID/STYRENE CROSSPOLYMER; BRAZIL NUT OIL; CRANBERRY SEED OIL; HONEY

Fruit of the Earth Cabana Beach Club with Manuka Honey and Essential Oils SPF 50 Sunscreen Lotion

Active Ingredients

Avobenzone 3.0%, Homosalate 10.0%, Octisalate 4.5%, Octocrylene 8.0%

Purpose

Sunscreen

Uses

• helps prevent sunburn • if used as directed with other sun protectino measures (see Directions), decreases the risk of skin cancer and early skin aging caused by the sun

Warnings

For external use only

Do not use

• on damaged or broken skin.

When using this product

• keep out of eyes. Rinse with water to remove.

Stop use and ask a doctor if

• if rash occurs.

Keep out of reach of children.

If swallowed, get medical help or contact a Poison Control Center right away.

Directions

- Apply liberally 15 minutes before sun exposure
- Reapply:

• after 80 minutes of swimming or sweating

• immediately after towel drying

• at least every 2 hours

- Children under 6 months of age: Ask a doctor
- Sun Protection Measures. Spending time in the sun increases your risk of skin cancer and early skin aging. To decrease this risk, regularly use a sunscreen with a Broad Spectrum SPF value of 15 or higher and other sun protection measures including:

• limit time in the sun, especially from 10 a.m. - 2 p.,.

• wear long-sleeved shirts, pants, hats, and sunglasses

Other information

- protect the product in this container from excessive heat and direct sun
- may stain or damage some fabrics, materials or surfaces

Inactive ingredients

Water, Polyester-7, Neopentyl Glycol Diheptanoate, Glycerin, Aluminum Starch Octenylsuccinate, Styrene/Acrylates Copolymer, Citrus Aurantium Dulcis (Orange) Peel Oil, Citrus Aurantifolia (Lime) Oil, Citrus sinensis (blood orange) oil, Silica, Phenoxyethanol, Isododecane, Arachidyl Alcohol, Beeswax, Ethylhexylglycerin, Acrylates/C10-30 Alkyl Acrylate Crosspolymer, Behenyl Alcohol, Tocopherol (Vitamin E), Arachidyl Glucoside, Glyceryl Stearate, PEG-100 Stearate, Potassium Hydroxide, Disodium EDTA, Sodium Ascorbyl Phosphate, Fragrance.